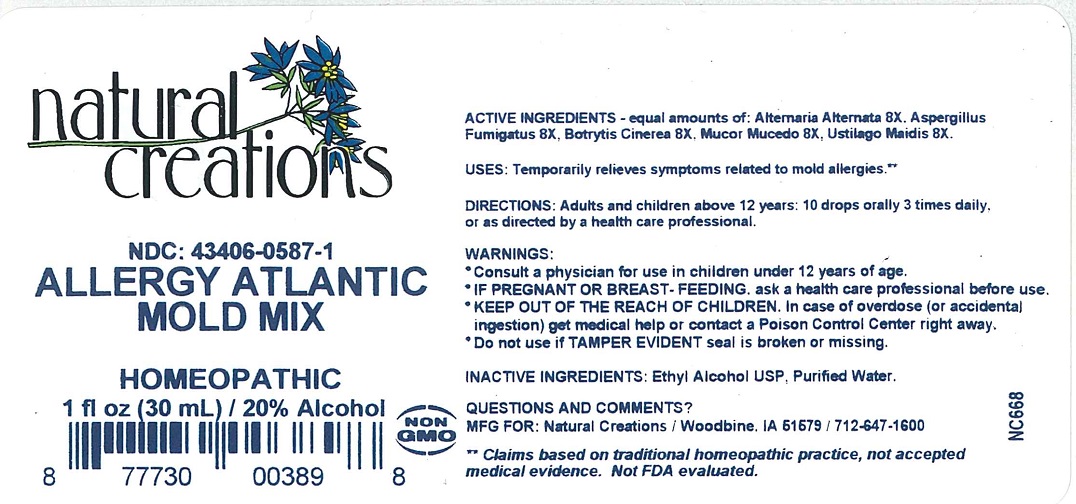 DRUG LABEL: ALLERGY ATLANTIC MOLD MIX
NDC: 43406-0587 | Form: LIQUID
Manufacturer: Natural Creations, Inc.
Category: homeopathic | Type: HUMAN OTC DRUG LABEL
Date: 20241219

ACTIVE INGREDIENTS: ALTERNARIA ALTERNATA 8 [hp_X]/1 mL; ASPERGILLUS FUMIGATUS 8 [hp_X]/1 mL; BOTRYTIS CINEREA 8 [hp_X]/1 mL; RHIZOPUS STOLONIFER 8 [hp_X]/1 mL; USTILAGO MAYDIS 8 [hp_X]/1 mL
INACTIVE INGREDIENTS: ALCOHOL; WATER

ALLERGY ATLANTIC MOLD MIX

ACTIVE INGREDIENT

ACTIVE INGREDIENTS - equal amounts of: Alternaria Alternata 8X, Aspergillus Fumigatus 8X, Botrytis Cinerea 8X, Mucor Mucedo 8X, Ustilago Maidis 8x.

PURPOSE

USES: Temporarily relieves symptoms related to mold allergies.**

INDICATIONS AND USAGE

USES: Temporarily relieves symptoms related to mold allergies.**

DOSAGE AND ADMINISTRATION

DIRECTIONS: Adults & children above 12 years: 10 drops orally 3 times daily, or as directed by a health care professional.

WARNINGS:

*Consult a physician for use in children under 12 years of age.

* IF PREGNANT OR BREAST-FEEDING, ask a health care professional before use.

* KEEP OUT OF THE REACH OF CHILDREN. In case of overdose (or accidental ingestion) get medical help or contact a Poison Control Center right away.

WARNINGS:

*Consult a physician for use in children under 12 years of age.

* IF PREGNANT OR BREAST-FEEDING, ask a health care professional before use.

* KEEP OUT OF THE REACH OF CHILDREN. In case of overdose (or accidental ingestion) get medical help or contact a Poison Control Center right away.

* Do not use if TAMPER EVIDENT seal is broken or missing.

INACTIVE INGREDIENTS: Ehtyl Alchohol USP, Purified Water.

QUESTIONS & COMMENTS?

Natural Creations, Inc. / Woodbine, IA 51579 / 712-647-1600

REFERENCES

** Claims based on traditional homeopathic practice, not accepted medical evidence. Not FDA evaluated.

PACKAGE LABEL

NDC: 43406-0587-1

ALLERGY ATLANTIC

MOLD MIX

HOMEOPATHIC

1 fl oz (30 mL) / 20% Alcohol

UPC: 877730003898 NON GMO Logo